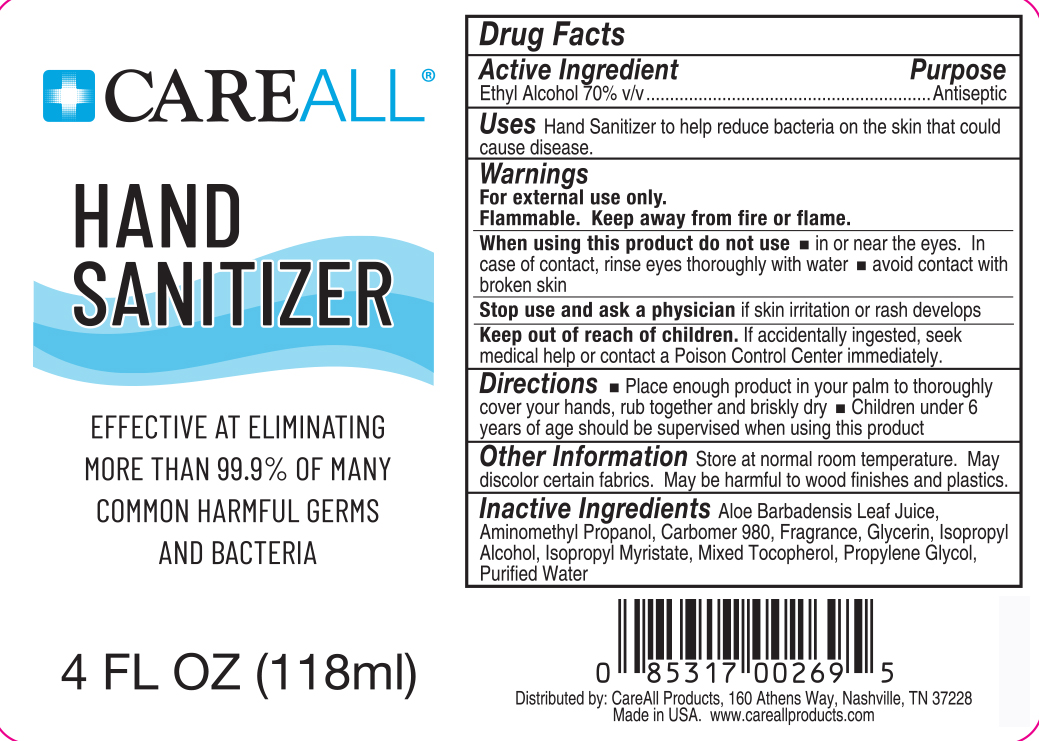 DRUG LABEL: CareALL Hand Sanitizer
NDC: 51824-110 | Form: GEL
Manufacturer: New World Imports, Inc.
Category: otc | Type: HUMAN OTC DRUG LABEL
Date: 20251201

ACTIVE INGREDIENTS: ALCOHOL 0.7 mL/1 mL
INACTIVE INGREDIENTS: GLYCERIN; ISOPROPYL ALCOHOL; ISOPROPYL MYRISTATE; PROPYLENE GLYCOL; WATER; TOCOPHEROL; ALOE VERA LEAF; AMINOMETHYLPROPANOL; CARBOMER HOMOPOLYMER TYPE C (ALLYL PENTAERYTHRITOL CROSSLINKED)

Instant Hand Sanitizer

Active ingredient

Ethyl Alcohol 70% v/v

Purpose

Antiseptic

Uses

Hand sanitizer to help reduce bacteria on the skin that could cause disease

Warnings

For external use only.

Flammable. Keep away from fire or flame.

When using this product do notuse in or near the eyes. In case of contact, rinse eyes thoroughly with water. Avoid contact with broken skin.

Stop use and ask a physicianif skin irritation or rash develops.

Keep out of reach of children.If accidently ingested, seek medical help or contact a Poison Control Center immediately.

Directions

Place enough product in your palm to thoroughly cover your hands, rub together briskly until dry. Children under 6 years of age should be supervised when using this product.

Other Information

Store at normal room temperature. May discolor certain fabrics. May be harmful to wood finishes and plastics

Inactive ingredients

Aloe Barbadenis Leaf Juice (Decolorized), Aminomethyl Propanol, Carbomer 980, Fragrance, Glycerin, Isopropyl Alcohol, Isopropyl Myristate, Mixed Tocopherol, Propylene Glycol, Purified Water,